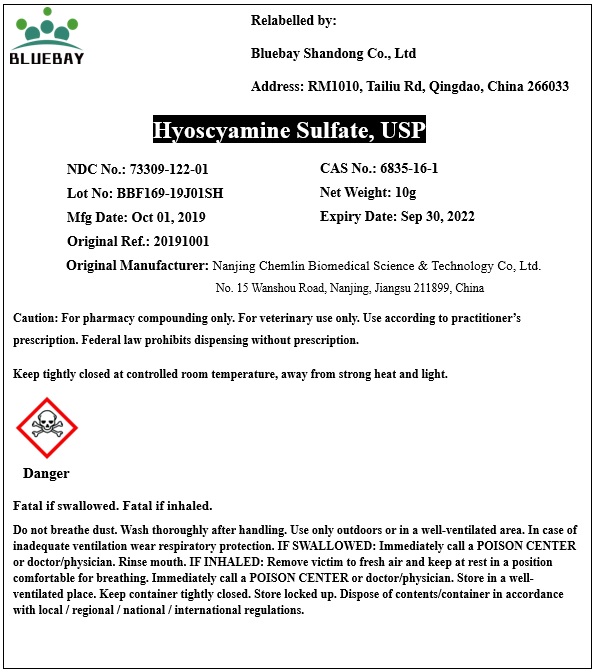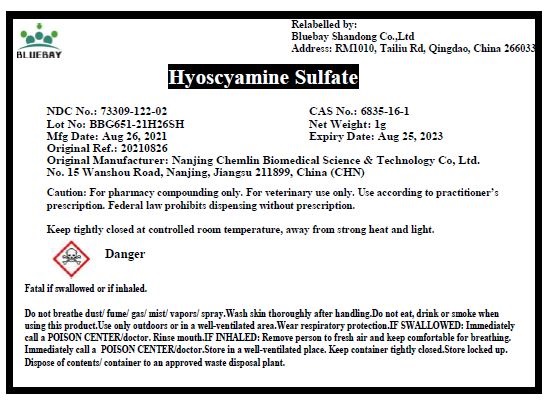 DRUG LABEL: Hyoscyamine Sulfate
NDC: 73309-122 | Form: POWDER
Manufacturer: BLUEBAY SHANDONG CO.,LTD
Category: other | Type: BULK INGREDIENT
Date: 20211214

ACTIVE INGREDIENTS: HYOSCYAMINE SULFATE 1 g/1 g

Hyoscyamine Sulfate